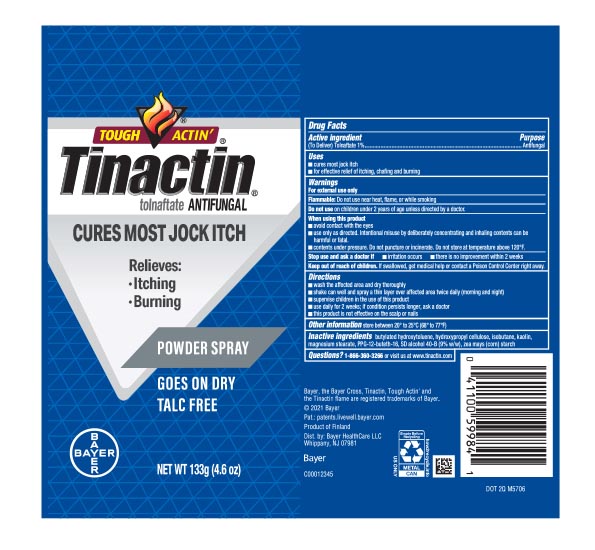 DRUG LABEL: Tinactin
NDC: 11523-0138 | Form: AEROSOL, POWDER
Manufacturer: Bayer HealthCare LLC
Category: otc | Type: HUMAN OTC DRUG LABEL
Date: 20251204

ACTIVE INGREDIENTS: TOLNAFTATE 10 mg/1 g
INACTIVE INGREDIENTS: BUTYLATED HYDROXYTOLUENE; ISOBUTANE; PPG-12-BUTETH-16; KAOLIN; MAGNESIUM STEARATE; STARCH, CORN; HYDROXYPROPYL CELLULOSE, UNSPECIFIED

Tinactin Jock Itch Powder Spray Talc Free

Drug Facts

Active ingredient

(To Deliver) Tolnaftate 1%

Purpose

Antifungal

Uses

- cures most jock itch
- for effective relief of itching, chafing and burning

Warnings

For external use only

Flammable: Do not use near heat, flame, or while smoking

Do not use on children under 2 years of age unless directed by a doctor.

When using this product

- avoid contact with the eyes
- use only as directed. Intentional misuse by deliberately concentrating and inhaling contents can be harmful or fatal
- contents under pressure. Do not puncture or incinerate. Do not store at temperature above 120°F.

Stop use and ask a doctor if

- irritation occurs
- there is no improvement within 2 weeks

Keep out of reach of children. If swallowed, get medical help or contact a Poison Control Center right away.

Directions

- wash affected area and dry thoroughly
- shake can well and spray a thin layer over affected area twice daily (morning and night)
- supervise children in the use of this product
- use daily for 2 weeks; if condition persists longer, ask a doctor
- this product is not effective on the scalp or nails

Other information

store between 20° to 25°C (68° to 77°F)

Inactive ingredients

butylated hydroxytoluene, hydroxypropyl cellulose, isobutane, kaolin, magnesium stearate, PPG-12-buteth-16, SD alcohol 40-B (9% w/w), zea mays (corn) starch

Questions?

1-866-360-3266 or visit us at www.tinactin.com

PRINCIPAL DISPLAY PANEL - 133g Can Label

TOUGH ACTIN' ®

Tinactin®

tolnaftate ANTIFUNGAL
Cures Most Jock Itch

Relieves:

- Itching
- Burning

POWDER SPRAY
Goes On Dry

Talc Free

NET WT 133g (4.6 oz)